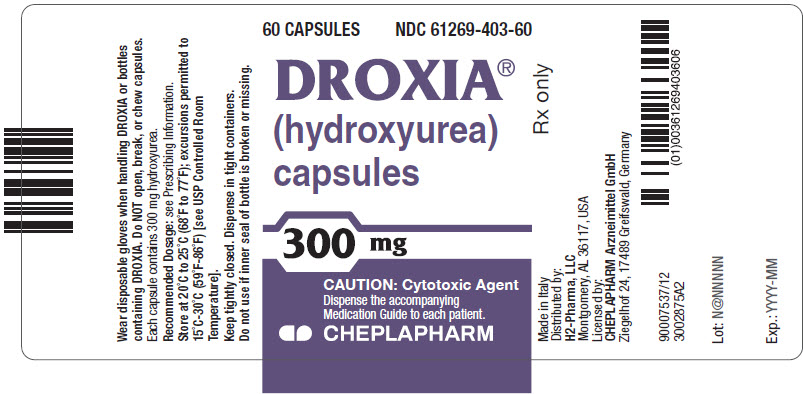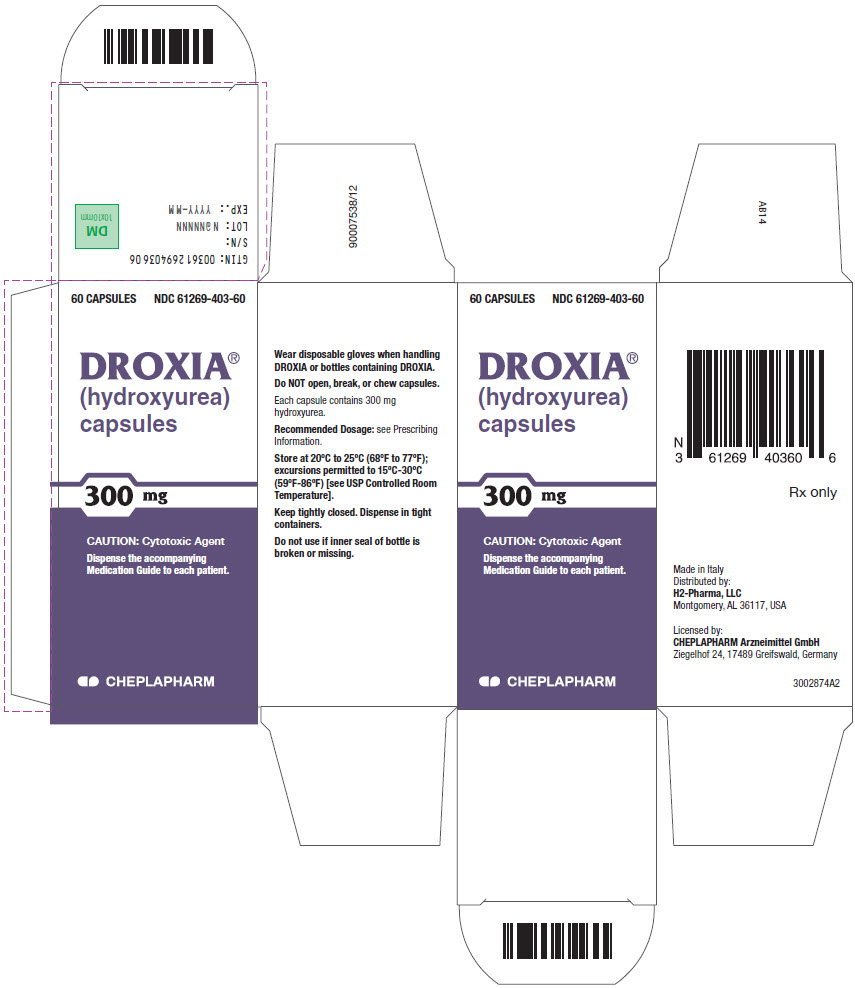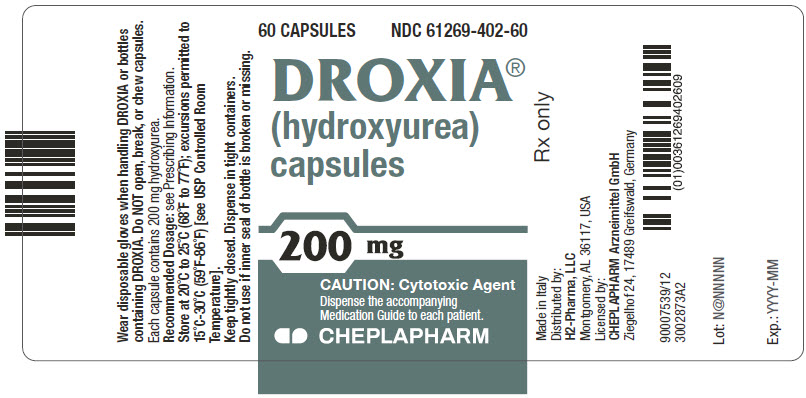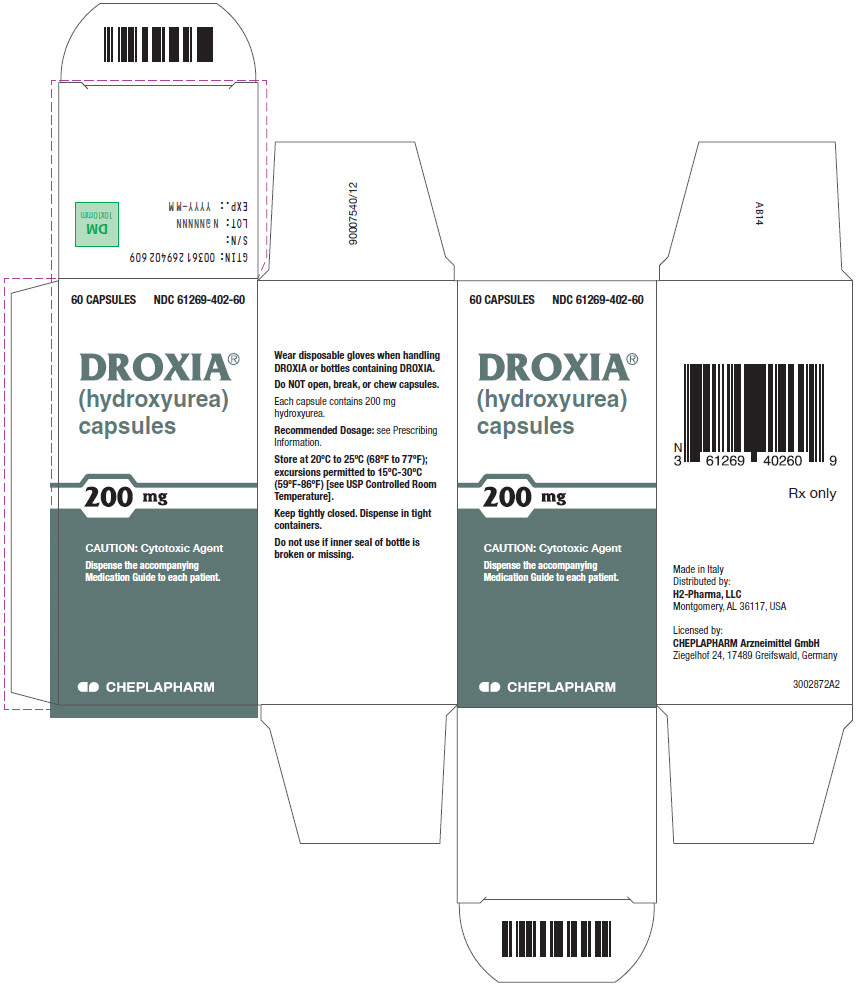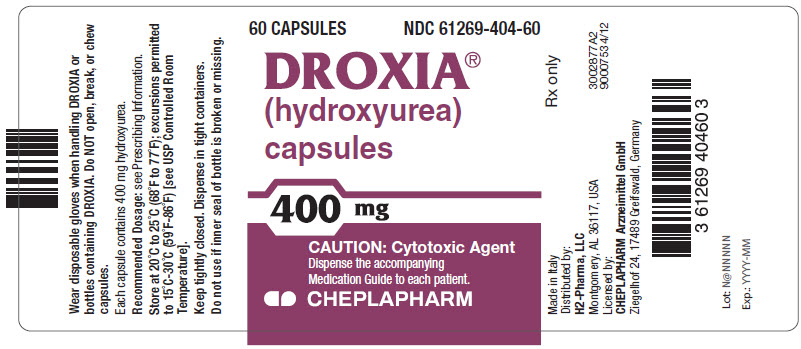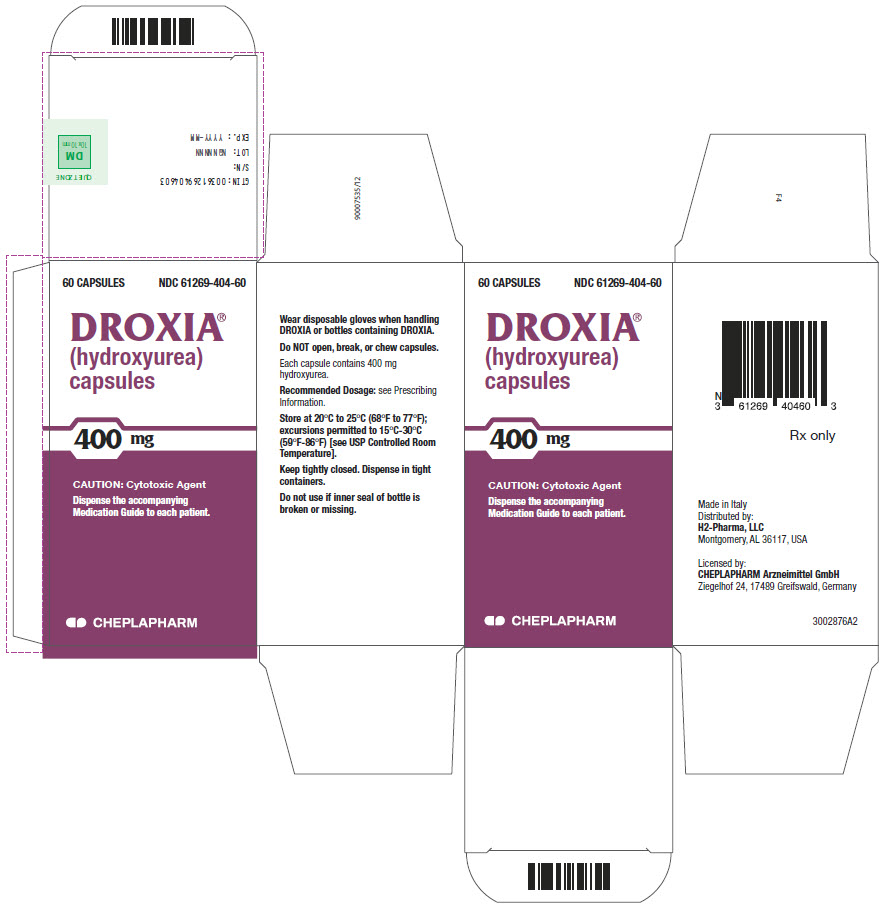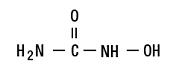 DRUG LABEL: DROXIA
NDC: 61269-403 | Form: CAPSULE
Manufacturer: H2-Pharma LLC
Category: prescription | Type: HUMAN PRESCRIPTION DRUG LABEL
Date: 20260126

ACTIVE INGREDIENTS: hydroxyurea 300 mg/1 1
INACTIVE INGREDIENTS: citric acid monohydrate; GELATIN, UNSPECIFIED; LACTOSE, UNSPECIFIED FORM; magnesium stearate; sodium phosphate; titanium dioxide; D&C Red No. 28; D&C Red No. 33; FD&C Blue No. 1

HIGHLIGHTS OF PRESCRIBING INFORMATION

These highlights do not include all the information needed to use DROXIA safely and effectively. See full prescribing information for DROXIA.
DROXIA (hydroxyurea) capsules, for oral use
Initial U.S. Approval: 1967

WARNING: MYELOSUPPRESSION AND MALIGNANCIES

See full prescribing information for complete boxed warning.

Myelosuppression: DROXIA may cause severe myelosuppression. Do not give if bone marrow function is markedly depressed. Monitor blood counts at baseline and throughout treatment. Interrupt treatment and reduce dose as necessary. (5.1)
Malignancies: DROXIA is carcinogenic. Advise sun protection and monitor patients for malignancies. (5.3)

RECENT MAJOR CHANGES

Warnings and Precautions, Laboratory Test Interference (5.10) 11/2023

Drug Interactions, Laboratory Test Interference (7.2) 11/2023

1 INDICATIONS AND USAGE

DROXIA is an antimetabolite indicated to reduce the frequency of painful crises and to reduce the need for blood transfusions in patients with sickle cell anemia with recurrent moderate to severe painful crises. (1)

2 DOSAGE AND ADMINISTRATION

- Initial dose: 15 mg/kg once daily. Monitor the patient's blood count every two weeks. (2.1)
- The dose may be increased by 5 mg/kg/day every 12 weeks until a maximum tolerated dose or 35 mg/kg/day is reached if blood counts are in an acceptable range. (2.1)
- The dose is not increased if blood counts are between the acceptable range and toxic. Discontinue DROXIA until hematologic recovery if blood counts are considered toxic. Treatment may then be resumed after reducing the dose by 2.5 mg/kg/day from the dose associated with hematological toxicity. (2.1)
- Renal impairment: Reduce the dose of DROXIA by 50% in patients with creatinine clearance less than 60 mL/min. (2.2, 8.6, 12.3)

3 DOSAGE FORMS AND STRENGTHS

•Capsules: 200 mg, 300 mg, and 400 mg (3)

4 CONTRAINDICATIONS

• In patients who have demonstrated a previous hypersensitivity to hydroxyurea or any other component of its formulation. (4)

5 WARNINGS AND PRECAUTIONS

- Hemolytic anemia: Monitor blood counts throughout treatment. If hemolysis persists, discontinue DROXIA. (5.2)
- Embryo-Fetal toxicity: Can cause fetal harm. Advise of potential risk to a fetus and use of effective contraception. (5.4, 8.1, 8.3)
- Vasculitic toxicities: Institute treatment and discontinue DROXIA if this occurs. (5.5)
- Live Vaccinations: Avoid live vaccine use in a patient taking DROXIA. (5.6)
- Risks with concomitant use of antiretroviral drugs: Pancreatitis, hepatotoxicity, and neuropathy have occurred. Monitor for signs and symptoms in patients with HIV infection using antiretroviral drugs; discontinue DROXIA and implement treatment. (5.7)

6 ADVERSE REACTIONS

Most common adverse reactions (≥30%) are hematological, gastrointestinal symptoms, and anorexia. (6)

To report SUSPECTED ADVERSE REACTIONS, contact CHEPLAPHARM Arzneimittel GmbH at 1-888-877-5884 or FDA at 1-800-FDA-1088 or www.fda.gov/medwatch.

7 DRUG INTERACTIONS

- Antiretroviral drugs. (7.1)
- Laboratory Test Interference. (7.2)

8 USE IN SPECIFIC POPULATIONS

Lactation: Advise women not to breastfeed. (8.2)

FULL PRESCRIBING INFORMATION

WARNING: MYELOSUPPRESSION AND MALIGNANCIES

Myelosuppression: DROXIA may cause severe myelosuppression. Do not give if bone marrow function is markedly depressed. Monitor blood counts at baseline and throughout treatment. Interrupt treatment and reduce dose as necessary [see Warnings and Precautions (5.1)].

Malignancies: DROXIA is carcinogenic. Advise sun protection and monitor patients for malignancies [see Warnings and Precautions (5.3)].

1 INDICATIONS AND USAGE

DROXIA is indicated to reduce the frequency of painful crises and to reduce the need for blood transfusions in patients with sickle cell anemia with recurrent moderate to severe painful crises.

2 DOSAGE AND ADMINISTRATION

2.1 Dosing Information

Table 1: Dosing Recommendation Based on Blood Count
Dosing Regimen | Dose | Dose Modification Criteria | Monitoring Parameters
Initial Recommended Dosing | 15 mg/kg/day as a single dose once daily based on the patient's actual or ideal weight, whichever is less. |  | Monitor the patient's blood count every 2 weeks [see Warnings and Precautions (5.1)].
Dosing Based on Blood Counts
In an acceptable range | Increase dose 5 mg/kg/day every 12 weeks; Maximal dose: 35 mg/kg/day*; *Maximal dose is the highest dose that does not produce toxic blood counts over 24 consecutive weeks. | Increase dosing only if blood counts are in an acceptable range.; Do not increase if myelosuppression occurs. | Blood Counts Acceptable Range; neutrophils ≥2500 cells/mm^3; platelets ≥95,000/mm^3; hemoglobin >5.3 g/dL; reticulocytes ≥95,000/mm^3 if the hemoglobin concentration <9 g/dL
Between acceptable and toxic range | Do not increase dose. | If blood counts are considered toxic, discontinue DROXIA until hematologic recovery. | Blood Counts Toxic Range; neutrophils <2000 cells/mm^3; platelets <80,000/mm^3; hemoglobin <4.5 g/dL; reticulocytes <80,000/mm^3 if the hemoglobin concentration <9 g/dL
Dosing After Hematologic Recovery | Reduce dose by 2.5 mg/kg/day. | Reduce the dose from the dose associated with hematologic toxicity.; May titrate up or down every 12 weeks in 2.5 mg/kg/day increments.; The patient should be at a stable dose with no hematologic toxicity for 24 weeks.; Discontinue the treatment permanently if a patient develops hematologic toxicity twice.

Swallow DROXIA capsules whole. Do NOT open, break, or chew capsules because DROXIA is a cytotoxic drug. Patients must be able to follow directions regarding drug administration and their monitoring and care.

Fetal hemoglobin (HbF) levels may be used to evaluate the efficacy of DROXIA in clinical use. Obtain HbF levels every three to four months. Monitor for an increase in HbF of at least two-fold over the baseline value.

DROXIA causes macrocytosis, which may mask the incidental development of folic acid deficiency. Prophylactic administration of folic acid is recommended.

DROXIA is a cytotoxic drug. Follow applicable special handling and disposal procedures [see References (15)].

2.2 Dose Modifications for Renal Impairment

Reduce the dose of DROXIA by 50% in patients with creatinine clearance of less than 60 mL/min or with end-stage renal disease (ESRD) [see Use in Specific Populations (8.6) and Clinical Pharmacology (12.3)]. Creatinine clearance values were obtained using 24-hour urine collections.

Creatinine Clearance; (mL/min) | Recommended DROXIA Initial Dose; (mg/kg once daily)
≥60 | 15
<60 or ESRD* | 7.5
* On dialysis days, administer DROXIA to patients with ESRD following hemodialysis.

Monitor the hematologic parameters closely in these patients.

3 DOSAGE FORMS AND STRENGTHS

Capsules:

- 200 mg opaque blue-green capsules, imprinted with black ink "DROXIA" and "200".
- 300 mg opaque purple capsules, imprinted with black ink "DROXIA" and "300".
- 400 mg opaque reddish-orange capsules, imprinted with black ink "DROXIA" and "400".

4 CONTRAINDICATIONS

DROXIA is contraindicated in patients who have demonstrated a previous hypersensitivity to hydroxyurea or any other component of its formulation.

5 WARNINGS AND PRECAUTIONS

5.1 Myelosuppression

Hydroxyurea causes severe myelosuppression. Treatment with DROXIA should not be initiated if bone marrow function is markedly depressed. Bone marrow suppression may occur, and leukopenia is generally its first and most common manifestation. Thrombocytopenia and anemia occur less often, and are seldom seen without a preceding leukopenia.

Some patients, treated at the recommended initial dose of 15 mg/kg/day, have experienced severe or life-threatening myelosuppression.

Evaluate hematologic status prior to and during treatment with DROXIA. Provide supportive care and modify dose or discontinue DROXIA as needed. Recovery from myelosuppression is usually rapid when therapy is interrupted.

5.2 Hemolytic Anemia

Cases of hemolytic anemia in patients treated with hydroxyurea for myeloproliferative diseases have been reported [see Adverse Reactions (6.1) ]. Patients who develop acute jaundice or hematuria in the presence of persistent or worsening of anemia should have laboratory tests evaluated for hemolysis (e.g., measurement of serum lactate dehydrogenase, haptoglobin, reticulocyte, unconjugated bilirubin levels, urinalysis, and direct and indirect antiglobulin [Coombs] tests). In the setting of confirmed diagnosis of hemolytic anemia and in the absence of other causes, discontinue DROXIA.

5.3 Malignancies

Hydroxyurea is a human carcinogen. In patients receiving long-term hydroxyurea for myeloproliferative disorders, secondary leukemia has been reported.

Secondary leukemia has also been reported in patients treated with long-term hydroxyurea for sickle cell disease. Leukemia has also been reported in patients with sickle cell disease and no prior history of treatment with hydroxyurea.

All patients using DROXIA should be followed up on a long-term basis with regular blood counts to detect development of leukemia.

Skin cancer has also been reported in patients receiving long-term hydroxyurea. Advise protection from sun exposure and monitor for the development of secondary malignancies.

5.4 Embryo-Fetal Toxicity

Based on the mechanism of action and findings in animals, DROXIA can cause fetal harm when administered to a pregnant woman. Hydroxyurea was embryotoxic and teratogenic in rats and rabbits at doses 0.8 times and 0.3 times, respectively, the maximum recommended human daily dose on a mg/m^2 basis. Advise pregnant women of the potential risk to a fetus [see Use in Specific Populations (8.1)].
Advise females of reproductive potential to use effective contraception during and after treatment with DROXIA for at least 6 months after therapy. Advise males of reproductive potential to use effective contraception during and after treatment with DROXIA for at least 1 year after therapy [see Use in Specific Populations (8.1, 8.3)].

5.5 Vasculitic Toxicities

Cutaneous vasculitic toxicities, including vasculitic ulcerations and gangrene, have occurred in patients with myeloproliferative disorders during therapy with hydroxyurea. These vasculitic toxicities were reported most often in patients with a history of, or currently receiving, interferon therapy. If cutaneous vasculitic ulcers occur, institute treatment and discontinue DROXIA.

5.6 Live Vaccinations

Avoid use of live vaccine in patients taking DROXIA. Concomitant use of DROXIA with a live virus vaccine may potentiate the replication of the virus and/or may increase the adverse reaction of the vaccine because normal defense mechanisms may be suppressed by DROXIA. Vaccination with live vaccines in a patient receiving DROXIA may result in severe infection. Patient's antibody response to vaccines may be decreased. Consider consultation with a specialist.

5.7 Risks with Concomitant Use of Antiretroviral Drugs

Pancreatitis, hepatotoxicity, and peripheral neuropathy have occurred when hydroxyurea was administered concomitantly with antiretroviral drugs, including didanosine and stavudine [see Drug Interactions (7.1)].

5.8 Macrocytosis

DROXIA may cause macrocytosis, which is self-limiting, and is often seen early in the course of treatment. The morphologic change resembles pernicious anemia, but is not related to vitamin B12 or folic acid deficiency. This may mask the diagnosis of pernicious anemia. Prophylactic administration of folic acid is recommended.

5.9 Pulmonary Toxicity

Interstitial lung disease including pulmonary fibrosis, lung infiltration, pneumonitis, and alveolitis/allergic alveolitis (including fatal cases) have been reported in patients treated for myeloproliferative neoplasm. Safety and effectiveness have not been established for the use of DROXIA in the treatment of myeloproliferative neoplasms and the use is not approved by the FDA. Monitor patients developing pyrexia, cough, dyspnea, or other respiratory symptoms frequently, investigate and treat promptly. Discontinue DROXIA and manage with corticosteroids. [see Adverse Reactions (6.1)].

5.10 Laboratory Test Interference

Interference with Uric Acid, Urea, or Lactic Acid Assays is possible, rendering falsely elevated results of these in patients treated with hydroxyurea [see Drug Interactions (7.2)].

Hydroxyurea may falsely elevate sensor glucose results from certain continuous glucose monitoring (CGM) systems and may lead to hypoglycemia if sensor glucose results are relied upon to dose insulin.
If a patient using a CGM is to be prescribed hydroxyurea, consult with the CGM prescriber about alternative glucose monitoring methods [see Drug Interactions (7.2)].

6 ADVERSE REACTIONS

The following clinically significant adverse reactions are described in detail in other labeling sections:

- Myelosuppression [see Warnings and Precautions (5.1)]
- Hemolytic anemia [see Warnings and Precautions (5.2)]
- Malignancies [see Warnings and Precautions (5.3)]
- Vasculitic toxicities [see Warnings and Precautions (5.5)]
- Risks with concomitant use of antiretroviral drugs [see Warnings and Precautions (5.7)]
- Macrocytosis [see Warnings and Precautions (5.8)]
- Pulmonary Toxicity [see Warnings and Precautions (5.9)]

Because clinical trials are conducted under widely varying conditions, adverse reaction rates observed in the clinical trials of a drug cannot be directly compared to rates in the clinical trials of another drug and may not reflect the rates observed in practice.

6.1 Clinical Trial Experience

In 299 patients treated for sickle cell anemia in the Multicenter Study of Hydroxyurea in Sickle Cell Anemia, the most common adverse reactions were hematologic, with neutropenia, and low reticulocyte and platelet levels necessitating temporary cessation in almost all patients. Hematologic recovery usually occurred in two weeks.

Other adverse reactions include hair loss, macrocytosis, bleeding, and melanonychia.

6.2 Postmarketing Experience

The following adverse reactions have been identified during post-approval use of hydroxyurea in the treatment of neoplastic diseases. Because these reactions are reported voluntarily from a population of uncertain size, it is not always possible to reliably estimate their frequency.

- Reproductive System and Breast disorders: azoospermia, and oligospermia
- Gastrointestinal disorders: stomatitis, nausea, vomiting, diarrhea, and constipation
- Metabolism and Nutrition disorders: anorexia
- Skin and subcutaneous tissue disorders: maculopapular rash, skin ulceration, cutaneous lupus erythematosus, dermatomyositis-like skin changes, peripheral and facial erythema, hyperpigmentation, nail hyperpigmentation, atrophy of skin and nails, scaling, violet papules, and alopecia
- Renal and urinary disorders: dysuria, elevations in serum uric acid, blood urea nitrogen (BUN), and creatinine levels
- Nervous system disorders: headache, dizziness, drowsiness, disorientation, hallucinations, and convulsions
- General disorders: fever, chills, malaise, edema, and asthenia
- Hepatobiliary disorders: elevation of hepatic enzymes, cholestasis, and hepatitis
- Respiratory disorders: diffuse pulmonary infiltrates, dyspnea, and pulmonary fibrosis, interstitial lung disease, pneumonitis, alveolitis, allergic alveolitis and cough
- Immune disorders: systemic lupus erythematosus
- Hypersensitivity: Drug-induced fever (pyrexia) (>39°C, >102°F) requiring hospitalization has been reported concurrently with gastrointestinal, pulmonary, musculoskeletal, hepatobiliary, dermatological or cardiovascular manifestations. Onset typically occurred within 6 weeks of initiation and resolved upon discontinuation of hydroxyurea. Upon re-administration fever re-occurred typically within 24 hours.
- Blood and lymphatic system disorders: hemolytic anemia

7 DRUG INTERACTIONS

7.1 Increased Toxicity with Concomitant Use of Antiretroviral Drugs

Pancreatitis

In patients with HIV infection during therapy with hydroxyurea and didanosine, with or without stavudine, fatal and nonfatal pancreatitis have occurred. Hydroxyurea is not indicated for the treatment of HIV infection; however, if patients with HIV infection are treated with hydroxyurea, and in particular, in combination with didanosine and/or stavudine, close monitoring for signs and symptoms of pancreatitis is recommended. Permanently discontinue therapy with DROXIA in patients who develop signs and symptoms of pancreatitis.

Hepatotoxicity

Hepatotoxicity and hepatic failure resulting in death have been reported during postmarketing surveillance in patients with HIV infection treated with hydroxyurea and other antiretroviral drugs. Fatal hepatic events were reported most often in patients treated with the combination of hydroxyurea, didanosine, and stavudine. Avoid this combination.

Peripheral Neuropathy

Peripheral neuropathy, which was severe in some cases, has been reported in patients with HIV infection receiving hydroxyurea in combination with antiretroviral drugs, including didanosine, with or without stavudine.

7.2 Laboratory Test Interference

Interference with Uric Acid, Urea, or Lactic Acid Assays

Studies have shown that there is an analytical interference of hydroxyurea with the enzymes (urease, uricase, and lactate dehydrogenase) used in the determination of urea, uric acid, and lactic acid, rendering falsely elevated results of these in patients treated with hydroxyurea.

Interference with Continuous Glucose Monitoring Systems

Hydroxyurea may falsely elevate sensor glucose results from certain continuous glucose monitoring (CGM) systems and may lead to hypoglycemia if sensor glucose results are relied upon to dose insulin.
If a patient using a CGM is to be prescribed hydroxyurea, consult with the CGM prescriber about alternative glucose monitoring methods.

8 USE IN SPECIFIC POPULATIONS

8.1 Pregnancy

Risk Summary

DROXIA can cause fetal harm based on findings from animal studies and the drug's mechanism of action [see Clinical Pharmacology (12.1)]. There are no data with DROXIA use in pregnant women to inform a drug-associated risk. In animal reproduction studies, administration of hydroxyurea to pregnant rats and rabbits during organogenesis produced embryotoxic and teratogenic effects at doses 0.8 times and 0.3 times, respectively, the maximum recommended human daily dose on a mg/m^2 basis (see Data). Advise women of the potential risk to a fetus and to avoid becoming pregnant while being treated with DROXIA.

In the U.S. general population, the estimated background risk of major birth defects and miscarriage in clinically recognized pregnancies is 2%–4% and 15%–20%, respectively.

Data

Animal Data

Hydroxyurea has been demonstrated to be a potent teratogen in a wide variety of animal models, including mice, hamsters, cats, miniature swine, dogs, and monkeys at doses within 1-fold of the human dose given on a mg/m^2 basis. Hydroxyurea is embryotoxic and causes fetal malformations (partially ossified cranial bones, absence of eye sockets, hydrocephaly, bipartite sternebrae, missing lumbar vertebrae) at 180 mg/kg/day (about 0.8 times the maximum recommended human daily dose on a mg/m^2 basis) in rats and at 30 mg/kg/day (about 0.3 times the maximum recommended human daily dose on a mg/m^2 basis) in rabbits. Embryotoxicity was characterized by decreased fetal viability, reduced live litter sizes, and developmental delays. Hydroxyurea crosses the placenta. Single doses of ≥375 mg/kg (about 1.7 times the maximum recommended human daily dose on a mg/m^2 basis) to rats caused growth retardation and impaired learning ability.

8.2 Lactation

Risk Summary

Hydroxyurea is excreted in human milk. Because of the potential for serious adverse reactions in a breastfed infant from hydroxyurea, including carcinogenicity, discontinue breastfeeding during treatment with DROXIA.

8.3 Females and Males of Reproductive Potential

Pregnancy Testing

Verify the pregnancy status of females of reproductive potential prior to initiating DROXIA therapy.

Contraception

Females

DROXIA can cause fetal harm when administered to a pregnant woman [see Use in Specific Populations (8.1)]. Advise females of reproductive potential to use effective contraception during and after treatment with DROXIA for at least 6 months after therapy. Advise females to immediately report pregnancy.

Males

DROXIA may damage spermatozoa and testicular tissue, resulting in possible genetic abnormalities. Males with female sexual partners of reproductive potential should use effective contraception during and after treatment with DROXIA for at least 1 year after therapy [see Nonclinical Toxicology (13.1)].

Infertility

Males

Based on findings in animals and humans, male fertility may be compromised by treatment with DROXIA. Azoospermia or oligospermia, sometimes reversible, has been observed in men. Inform male patients about the possibility of sperm conservation before the start of therapy [see Adverse Reactions (6) and Nonclinical Toxicology (13.1)].

8.4 Pediatric Use

Safety and effectiveness in pediatric patients have not been established.

8.5 Geriatric Use

Clinical studies of DROXIA did not include sufficient numbers of subjects aged 65 and over to determine whether they respond differently from younger subjects.

Elderly patients may be more sensitive to the effects of hydroxyurea and may require a lower dose regimen. Hydroxyurea is excreted by the kidney, and the risk of adverse reactions to this drug may be greater in patients with impaired renal function. Because elderly patients are more likely to have decreased renal function, care should be taken in dose selection, and it may be useful to monitor renal function [see Dosage and Administration (2.2)].

8.6 Renal Impairment

The exposure to hydroxyurea is higher in patients with creatinine clearance of less than 60 mL/min. Reduce dosage and closely monitor the hematologic parameters when DROXIA is to be administered to these patients [see Dosage and Administration (2.2) and Clinical Pharmacology (12.3)].

8.7 Hepatic Impairment

There are no data that support specific guidance for dosage adjustment in patients with hepatic impairment. Close monitoring of hematologic parameters is advised in these patients.

10 OVERDOSAGE

Acute mucocutaneous toxicity has been reported in patients receiving hydroxyurea at dosages several times the therapeutic dose. Soreness, violet erythema, edema on palms and soles followed by scaling of hands and feet, severe generalized hyperpigmentation of the skin, and stomatitis have been observed.

11 DESCRIPTION

DROXIA® (hydroxyurea capsules, USP) is available for oral use as capsules containing 200 mg, 300 mg, and 400 mg hydroxyurea. Inactive ingredients include citric acid, gelatin, lactose, magnesium stearate, sodium phosphate, titanium dioxide, and capsule colorants: FD&C Blue No. 1 and FD&C Green No. 3 (200 mg capsules); D&C Red No. 28, D&C Red No. 33, and FD&C Blue No. 1 (300 mg capsules); D&C Red No. 28, D&C Red No. 33, and D&C Yellow No. 10 (400 mg capsules).

Hydroxyurea is a white to off-white crystalline powder. It is hygroscopic and freely soluble in water, but practically insoluble in alcohol. The empirical formula is CH4N2O2 and it has a molecular weight of 76.05. Its structural formula is:

12 CLINICAL PHARMACOLOGY

12.1 Mechanism of Action

The precise mechanism by which hydroxyurea produces its cytotoxic and cytoreductive effects is not known. However, various studies support the hypothesis that hydroxyurea causes an immediate inhibition of DNA synthesis by acting as a ribonucleotide reductase inhibitor, without interfering with the synthesis of ribonucleic acid or of protein.

The mechanisms by which DROXIA produces its beneficial effects in patients with sickle cell anemia (SCA) are uncertain. Known pharmacologic effects of DROXIA that may contribute to its beneficial effects include increasing hemoglobin F levels in red blood cells (RBCs), decreasing neutrophils, increasing the water content of RBCs, increasing deformability of sickled cells, and altering the adhesion of RBCs to endothelium.

12.3 Pharmacokinetics

Absorption

Following oral administration of DROXIA, hydroxyurea reaches peak plasma concentrations in 1 to 4 hours. Mean peak plasma concentrations and AUCs increase more than proportionally with increase of dose.

There are no data on the effect of food on the absorption of hydroxyurea.

Distribution

Hydroxyurea distributes throughout the body with a volume of distribution approximating total body water.

Hydroxyurea concentrates in leukocytes and erythrocytes.

Metabolism

Up to 60% of an oral dose undergoes conversion through saturable hepatic metabolism and a minor pathway of degradation by urease found in intestinal bacteria.

Excretion

In patients with sickle cell anemia, the mean cumulative urinary recovery of hydroxyurea was about 40% of the administered dose.

Specific Populations

Renal Impairment

The effect of renal impairment on the pharmacokinetics of hydroxyurea was assessed in adult patients with sickle cell disease and renal impairment. Patients with normal renal function (creatinine clearance [CrCl] >80 mL/min), mild (CrCl 50-80 mL/min), moderate (CrCl =30-<50 mL/min), or severe (<30 mL/min) renal impairment received a single oral dose of 15 mg/kg hydroxyurea. Creatinine clearance values were obtained using 24-hour urine collections. Patients with ESRD received two doses of 15 mg/kg separated by 7 days; the first was given following a 4-hour hemodialysis session, the second prior to hemodialysis. The exposure to hydroxyurea (mean AUC) in patients with CrCl <60 mL/min and those with ESRD was 64% higher than in patients with normal renal function (CrCl >60 mL/min). Reduce the dose of DROXIA when it is administered to patients with creatinine clearance of <60 mL/min or with ESRD following hemodialysis [see Dosage and Administration (2.2) and Use in Specific Populations (8.6)].

13 NONCLINICAL TOXICOLOGY

13.1 Carcinogenesis, Mutagenesis, Impairment of Fertility

Conventional long-term studies to evaluate the carcinogenic potential of DROXIA have not been performed. However, intraperitoneal administration of 125 to 250 mg/kg hydroxyurea (about 0.6-1.2 times the maximum recommended human oral daily dose on a mg/m^2 basis) thrice weekly for 6 months to female rats increased the incidence of mammary tumors in rats surviving to 18 months compared to control. Hydroxyurea is mutagenic in vitro to bacteria, fungi, protozoa, and mammalian cells. Hydroxyurea is clastogenic in vitro (hamster cells, human lymphoblasts) and in vivo (SCE assay in rodents, mouse micronucleus assay). Hydroxyurea causes the transformation of rodent embryo cells to a tumorigenic phenotype.

Hydroxyurea administered to male rats at 60 mg/kg/day (about 0.3 times the maximum recommended human daily dose on a mg/m^2 basis) produced testicular atrophy, decreased spermatogenesis, and significantly reduced their ability to impregnate females.

14 CLINICAL STUDIES

The efficacy of DROXIA in sickle cell anemia was assessed in a large clinical study (Multicenter Study of Hydroxyurea in Sickle Cell Anemia) (see Table 2).

The study was a randomized, double-blind, placebo-controlled trial that evaluated 299 adult patients (≥18 years) with moderate to severe disease (≥3 painful crises yearly). The trial was stopped by the Data Safety Monitoring Committee, after accrual was completed but before the scheduled 24 months of follow-up was completed in all patients, based on observations of fewer painful crises among patients receiving hydroxyurea.

Compared to placebo treatment, treatment with hydroxyurea resulted in a significant decrease in the yearly rate of painful crises, the yearly rate of painful crises requiring hospitalization, the incidence of chest syndrome, the number of patients transfused, and units of blood transfused. Hydroxyurea treatment significantly increased the median time to both first and second painful crises.

Although patients with 3 or more painful crises during the preceding 12 months were eligible for the study, most of the benefit in crisis reduction was seen in the patients with 6 or more painful crises during the preceding 12 months.

Table 2: Results from the Multicenter Study of Hydroxyurea in Sickle Cell Anemia
Event | Hydroxyurea (N=152) | Placebo (N=147) | Percent Change Versus Placebo | P-value
Median yearly rate of painful crises* | 2.5 | 4.6 | −46 | =0.001
Median yearly rate of painful crises requiring hospitalization | 1.0 | 2.5 | −60 | =0.0027
Median time to first painful crisis (months) | 2.76 | 1.35 | +104 | =0.014
Median time to second painful crisis (months) | 6.58 | 4.13 | +59 | =0.0024
Incidence of chest syndrome (# episodes) | 56 | 101 | −45 | =0.003
Number of patients transfused | 55 | 79 | −30 | =0.002
Number of units of blood transfused | 423 | 670 | −37 | =0.003
* A painful crisis was defined in the study as acute sickling-related pain that resulted in a visit to a medical facility, that lasted more than 4 hours, and that required treatment with a parenteral narcotic or NSAID. Chest syndrome, priapism, and hepatic sequestration were also included in this definition.

In patients with SCA treated with hydroxyurea, fetal hemoglobin (HbF) increases 4 to 12 weeks after initiation of treatment. In general, average HbF levels correlate with dose and plasma level with possible plateauing at higher dosages.

A clear relation between reduction in crisis frequency and increased HbF or F-cell levels has not been demonstrated. The dose-related cytoreductive effects of hydroxyurea, particularly on neutrophils, was the factor most strongly correlated with reduced crisis frequency.

15 REFERENCES

OSHA. http://www.osha.gov/SLTC/hazardousdrugs/index.html.

16 HOW SUPPLIED/STORAGE AND HANDLING

16.1 How Supplied

DROXIA® (hydroxyurea capsules, USP) is supplied in HDPE bottles with a plastic safety screw cap. Each bottle contains 60 capsules. DROXIA is supplied in the following strengths:

200 mg opaque blue-green capsules, marked in black ink with "DROXIA" and "200" (NDC 61269-402-60).

300 mg opaque purple capsules, marked in black ink with "DROXIA" and "300" (NDC 61269-403-60).

400 mg opaque reddish-orange capsules, marked in black ink with "DROXIA" and "400" (NDC 61269-404-60).

16.2 Storage

Store at 20°C to 25°C (68°F to 77°F); excursions permitted to 15°C to 30°C (59°F to 86°F) [see USP Controlled Room Temperature]. Keep tightly closed.

16.3 Handling and Disposal

DROXIA is a cytotoxic drug. Follow applicable special handling and disposal procedures [see References (15)].

To decrease the risk of contact, advise caregivers to wear disposable gloves when handling DROXIA or bottles containing DROXIA. Wash hands with soap and water before and after contact with the bottle or capsules when handling DROXIA. Do not open DROXIA capsules. Avoid exposure to crushed or opened capsules. If contact with crushed or opened capsules occurs on the skin, wash affected area immediately and thoroughly with soap and water. If contact with crushed or opened capsules occurs on the eye(s), the affected area should be flushed thoroughly with water or isotonic eyewash designated for that purpose for at least 15 minutes. If the powder from the capsule is spilled, immediately wipe it up with a damp disposable towel and discard in a closed container, such as a plastic bag; as should the empty capsules. The spill areas should then be cleaned three times using a detergent solution followed by clean water. Keep the medication away from children and pets. Contact your doctor for instructions on how to dispose of outdated capsules.

17 PATIENT COUNSELING INFORMATION

Advise the patient to read the FDA-approved patient labeling (Medication Guide).

- There is a risk of myelosuppression. Monitoring blood counts every two weeks throughout the duration of therapy should be emphasized to patients taking DROXIA. Advise patients to report signs and symptoms of infection or bleeding immediately [see Warnings and Precautions (5.1)].
- Advise patients of the risk of hemolytic anemia. Advise patients that they will have blood tests to evaluate for this if they develop persistent anemia. [see Warnings and Precautions (5.2)].
- Advise patients that there is a risk of cutaneous vasculitic toxicities and secondary malignancies including leukemia and skin cancers. Advise use of sun protection [see Warnings and Precautions (5.3, 5.5)].
- Advise patients to inform their healthcare provider if they have received or are planning to receive vaccinations while taking DROXIA as this may result in a severe infection [see Warnings and Precautions (5.6)].
- Advise patients to notify their healthcare provider if they are using a continuous glucose monitoring system while taking DROXIA [see Warnings and Precautions (5.10)].
- Advise females of reproductive potential of the potential risk to a fetus and to inform their healthcare provider of a known or suspected pregnancy. Advise females and males of reproductive potential to use contraception during and after treatment with DROXIA [see Warnings and Precautions (5.4) and Use in Specific Populations (8.1, 8.3)].
- Advise females to discontinue breastfeeding during treatment with DROXIA [see Use in Specific Populations (8.2)].
- Patients with HIV infection should contact their physician for signs and symptoms of pancreatitis, hepatic events, and peripheral neuropathy [see Warnings and Precautions (5.7)].
- Advise patients of the symptoms of potential pulmonary toxicity and instruct them to seek prompt medical attention in the event of pyrexia, cough, dyspnea, or other respiratory symptoms [see Warnings and Precautions (5.9)].

Distributed by:
H2-Pharma, LLC
Montgomery, AL 36117, USA

Licensed by:
CHEPLAPHARM Arzneimittel GmbH
Ziegelhof 24, 17489 Greifswald, Germany

© 2023 CHEPLAPHARM Arzneimittel GmbH. All rights reserved.

Medication Guide
DROXIA® (drock-SEE-yuh)
(hydroxyurea)
capsules

What is the most important information I should know about DROXIA?
DROXIA can cause serious side effects including:

- Low blood counts are common with DROXIA, including low red blood cells, white blood cells, and platelets, and can be severe and life-threatening. If your white blood cell count becomes very low, you are at increased risk for infection. Your healthcare provider will check your blood cell counts before and during treatment with DROXIA. Your healthcare provider may change your dose or tell you to stop taking DROXIA if you have low blood cell counts. Tell your healthcare provider right away if you get any of the following symptoms:

- Fever

- feeling very tired

- chills

- shortness of breath

- body aches

- bleeding or unexplained bruising

- Cancer. Some people have developed cancer, such as leukemia and skin cancer, after taking DROXIA for a long time. Your healthcare provider will check you for cancer. You should protect your skin from the sun using sunblock, hats, and sun-protective clothing.

- DROXIA can harm your unborn baby.

For females taking DROXIA who can become pregnant:

- You should talk with your healthcare provider about the risks of DROXIA to your unborn baby.
- You should use effective birth control during treatment with DROXIA and for at least 6 months after treatment.
- Your healthcare provider will perform a pregnancy test before you start treatment with DROXIA.
- You should avoid becoming pregnant during treatment with DROXIA. Tell your healthcare provider right away if you become pregnant or think you may be pregnant.

For males taking DROXIA:

- DROXIA can affect your sperm. If you have a female sexual partner who can become pregnant, you should use a condom during treatment with DROXIA and for at least 1 year after treatment.

DROXIA may cause fertility problems in males. Talk to your healthcare provider if this is a concern for you.

See "What are the possible side effects of DROXIA?" for more information about side effects.

What is DROXIA?
DROXIA is a prescription medicine that is used to reduce the frequency of painful crises and reduce the need for blood transfusions in people with sickle cell anemia with recurrent moderate to severe painful crises.
It is not known if DROXIA is safe and effective in children.

Do not take DROXIA if you are allergic to hydroxyurea or any of the ingredients in DROXIA. See the end of this leaflet for a list of the ingredients in DROXIA.

Before taking DROXIA, tell your healthcare provider about all of your medical conditions, including if you:

- are using a continuous glucose monitor (CGM) to test your blood glucose. Hydroxyurea may affect your sensor glucose results and may lead to low blood sugar (hypoglycemia). Talk to the healthcare provider that prescribed your CGM about whether it is safe to use while you are taking DROXIA.
- have kidney problems or are receiving hemodialysis.
- have human immunodeficiency virus (HIV). Taking DROXIA with certain HIV medicines can cause serious reactions and may lead to death. Tell your healthcare provider if you take an HIV medicine.
- have increased level of uric acid in your blood (hyperuricemia).
- have a history of receiving interferon therapy or are currently receiving interferon therapy.
- have leg wounds or ulcers
- plan to receive any vaccinations. You should not receive "live vaccines" during treatment with DROXIA.
- are pregnant or plan to become pregnant. See "What is the most important information I should know about DROXIA?"
- are breastfeeding or plan to breastfeed. DROXIA can pass into your breast milk. Do not breastfeed during treatment with DROXIA.

Tell your healthcare provider about all the medicines you take, including prescription and over-the-counter medicines, vitamins, and herbal supplements.

How should I take DROXIA?

- Take DROXIA exactly as your healthcare provider tells you. DROXIA is taken 1 time a day.
- If you take too much DROXIA, call your healthcare provider or go to the nearest hospital emergency room right away.
- DROXIA capsules must be handled with care. To decrease the risk of exposure, you or your caregivers should do the following when handling DROXIA:

- Wear disposable gloves when handling DROXIA capsules or bottles containing DROXIA.
- Wash your hands with soap and water before and after handling DROXIA capsules or bottles containing DROXIA.
- Do NOT open, break, or chew the capsules.
- Avoid contact with crushed or opened capsules. If contact from crushed or opened capsules happens on the skin, wash the skin area right away and thoroughly with soap and water. If contact from crushed or opened capsules happens in the eyes, flush the eyes thoroughly with water or isotonic eyewash used for that purpose for at least 15 minutes.
- If the powder from the capsule is spilled, wipe it up right away with a damp disposable towel. Throw the damp disposable towel and the empty capsules away in a closed container, such as a plastic bag. The spill areas should then be cleaned three times using a detergent solution followed by clean water.

What are the possible side effects of DROXIA?
DROXIA may cause serious side effects, including:

- See "What is the most important information I should know about DROXIA?"
- Skin ulcers and death of tissue (gangrene) have happened in people who take DROXIA. This has happened most often in people who receive interferon therapy or have a history of interferon therapy. Your healthcare provider will stop treatment with DROXIA if you develop any skin ulcers.
- Enlarged red blood cells (macrocytosis). Macrocytosis is common in people who take DROXIA and can make it difficult to detect a decrease of folic acid. Your healthcare provider may prescribe a folic acid supplement for you.
- Hemolytic Anemia, the fast breakdown of red blood cells, has happened in people who take DROXIA. Tell your healthcare provider if you develop yellowing of your skin (jaundice) or blood in your urine. Your healthcare provider may do blood tests if you have persistent or worsening anemia.
- Respiratory (breathing) problems. Some people have developed life-threatening respiratory conditions called interstitial lung disease. Your healthcare provider may tell you to stop taking DROXIA if you develop respiratory problems. Tell your healthcare provider right away if you get any of the following symptoms:

- fever

- shortness of breath

- cough

The most common side effects of DROXIA include:

- reduced blood counts
- bleeding
- mouth ulcers
- nausea
- diarrhea or constipation
- loss of appetite

These are not all the possible side effects of DROXIA.
Call your doctor for medical advice about side effects. You may report side effects to FDA at 1-800-FDA-1088.

How should I store DROXIA?

- Store DROXIA at room temperature between 68°F to 77°F (20°C to 25°C).
- Keep the DROXIA bottle tightly closed.
- Call your healthcare provider for instructions on how to throw away (dispose of) DROXIA that is out of date.

Keep DROXIA and all medicines out of the reach of children. Keep DROXIA away from pets.

General information about the safe and effective use of DROXIA
Medicines are sometimes prescribed for purposes other than those listed in a Medication Guide. Do not use DROXIA for a condition for which it was not prescribed. Do not give DROXIA to other people, even if they have the same symptoms you have. It may harm them. You can ask your healthcare provider or pharmacist for information about DROXIA that is written for health professionals.

What are the ingredients of DROXIA?
Active ingredient: hydroxyurea
Inactive ingredients: citric acid, gelatin, lactose, magnesium stearate, sodium phosphate, titanium dioxide, and capsule colorants: FD&C Blue No. 1 and FD&C Green No. 3 (200 mg capsules); D&C Red No. 28, D&C Red No. 33, and FD&C Blue No. 1 (300 mg capsules); D&C Red No. 28, D&C Red No. 33, and D&C Yellow No. 10 (400 mg capsules).

Distributed by:
H2-Pharma, LLC, Montgomery, AL 36117, USA

Licensed by:
CHEPLAPHARM Arzneimittel GmbH, Ziegelhof 24, 17489
Greifswald, Germany
© 2023 CHEPLAPHARM Arzneimittel GmbH. All rights
reserved.
For more information call 1-888-877-5884.

This Medication Guide has been approved by the U.S. Food and Drug Administration.

Revised: November 2023

PRINCIPAL DISPLAY PANEL - 300 mg Capsule Bottle Label

60 CAPSULES
NDC 61269-403-60

DROXIA®
(hydroxyurea)
capsules

300 mg

CAUTION: Cytotoxic Agent

Dispense the accompanying
Medication Guide to each patient.

CHEPLAPHARM

PRINCIPAL DISPLAY PANEL - 300 mg Capsule Bottle Carton

60 CAPSULES
NDC 61269-403-60

DROXIA®
(hydroxyurea)
capsules

300 mg

CAUTION: Cytotoxic Agent

Dispense the accompanying
Medication Guide to each patient.

CHEPLAPHARM

PRINCIPAL DISPLAY PANEL - 200 mg Capsule Bottle Label

60 CAPSULES
NDC 61269-402-60

DROXIA®
(hydroxyurea)
capsules

200 mg

CAUTION: Cytotoxic Agent

Dispense the accompanying
Medication Guide to each patient.

CHEPLAPHARM

PRINCIPAL DISPLAY PANEL - 200 mg Capsule Bottle Carton

60 CAPSULES
NDC 61269-402-60

DROXIA®
(hydroxyurea)
capsules

200 mg

CAUTION: Cytotoxic Agent

Dispense the accompanying
Medication Guide to each patient.

CHEPLAPHARM

PRINCIPAL DISPLAY PANEL - 400 mg Capsule Bottle Label

60 CAPSULES
NDC 61269-404-60

DROXIA®
(hydroxyurea)
capsules

400 mg

CAUTION: Cytotoxic Agent

Dispense the accompanying
Medication Guide to each patient.

CHEPLAPHARM

PRINCIPAL DISPLAY PANEL - 400 mg Capsule Bottle Carton

60 CAPSULES
NDC 61269-404-60

DROXIA®
(hydroxyurea)
capsules

400 mg

CAUTION: Cytotoxic Agent

Dispense the accompanying
Medication Guide to each patient.

CHEPLAPHARM